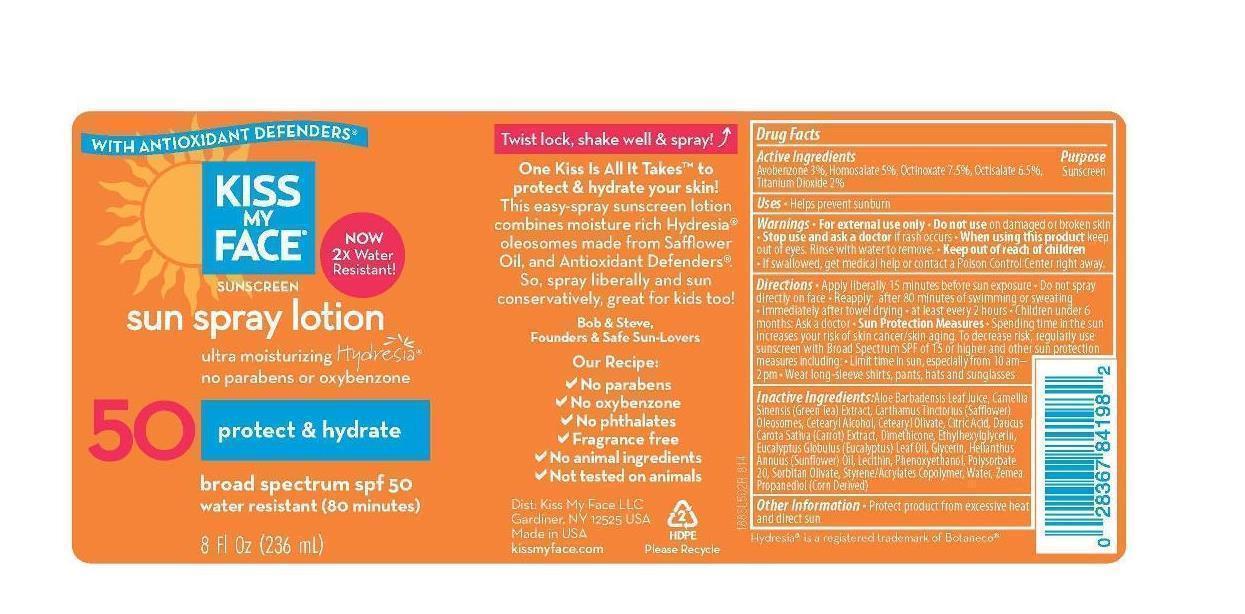 DRUG LABEL: Sunspray
NDC: 65364-218 | Form: SPRAY
Manufacturer: Kiss My Face, LLC
Category: otc | Type: HUMAN OTC DRUG LABEL
Date: 20150127

ACTIVE INGREDIENTS: AVOBENZONE 3 g/100 g; HOMOSALATE 5 g/100 g; OCTINOXATE 7.5 g/100 g; OCTISALATE 6.5 g/100 g; TITANIUM DIOXIDE 2 g/100 g
INACTIVE INGREDIENTS: water; GREEN TEA LEAF; ALOE VERA LEAF; CARTHAMUS TINCTORIUS (SAFFLOWER) OLEOSOMES; CETOSTEARYL ALCOHOL; CETEARYL OLIVATE; CITRIC ACID ACETATE; DAUCUS CAROTA SUBSP. CAROTA WHOLE; DIMETHICONE; EUCALYPTUS GUNNII LEAF OIL; GLYCERIN; SUNFLOWER OIL; LECITHIN, SOYBEAN; PHENOXYETHANOL; POLYSORBATE 20; SORBITAN OLIVATE; STYRENE/ACRYLAMIDE COPOLYMER (MW 500000); PROPANEDIOL

Sunspray Lotion

Active ingredients

Avobenzone (3.0%), Homosalate (5.0%), Octinoxate (7.5%), Octisalate (6.5%), Titanium Dioxide (2.0%).

Inactive ingredients

Aloe Barbadensis Leaf Juice, Camellia Sinensis (Green Tea) Extract, Carthamus Tinctorius (Safflower) Oleosomes, Cetearyl Alcohol, Cetearyl Olivate, Citric Acid, Daucus Carota Sativa (Carrot) Extract, Dimethicone, Ethylhexylglycerin, Eucalyptus Globulus Oil, Glycerin, Helianthus Annuus (Sunflower) Oil, Lecithin, Phenoxyethanol, Polysorbate-20, Sorbitan Olivate, Styrene/Acrylates Copolymer, Water, Zemea Propanediol.

Keep out of reach of children

Directions

Apply liberally 15 minutes before sun exposure

Do not spray directly on face

Reapply ater 80 minutes of swimming or sweating, immediately after towel drying, at least ever 2 hours

Children under 6 months ask a doctor

Use

Helps prevent sunburn

Purpose

sunscreen

Warnings

Do not use on damaged or broken skin

Stop use and ask doctor if rash occurs

When using this product keep out of eyes. Rinse with water to remove.

If swallowed get medical help or contact a poison control center right away